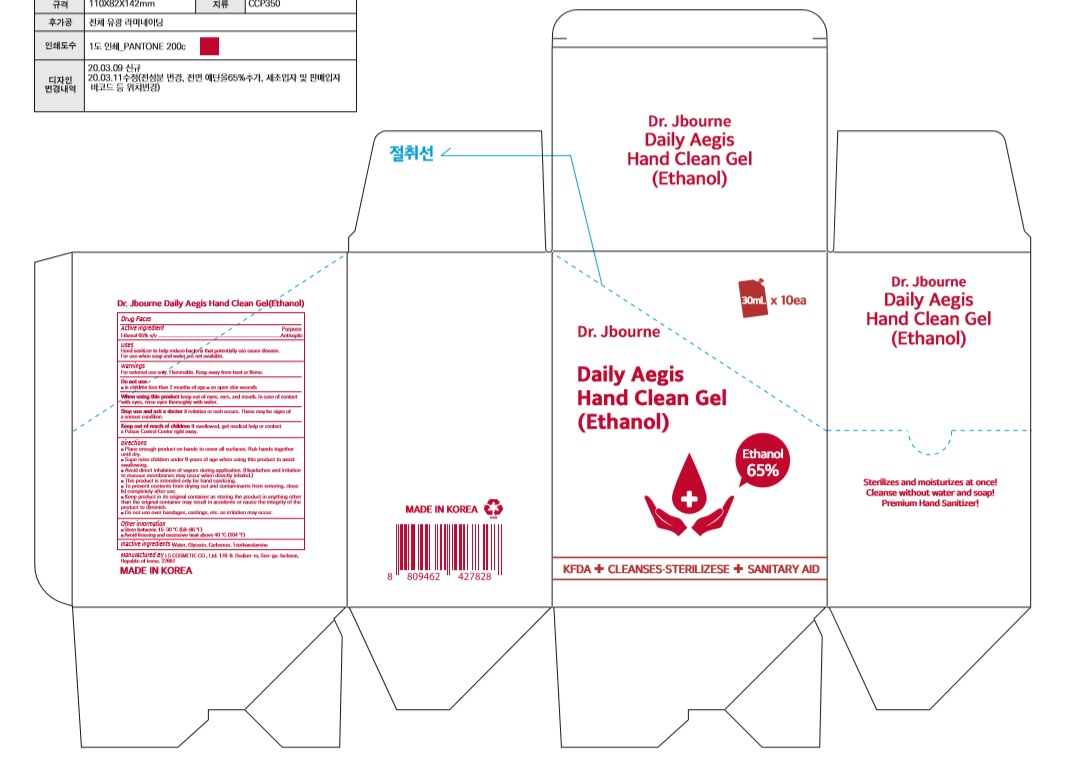 DRUG LABEL: Dr. Jbourne Daily Aegis Hand Clean Gel(Ethanol)
NDC: 59545-0365 | Form: GEL
Manufacturer: LS COSMETIC CO.,LTD.
Category: otc | Type: HUMAN OTC DRUG LABEL
Date: 20200413

ACTIVE INGREDIENTS: ALCOHOL 19.5 mL/30 mL
INACTIVE INGREDIENTS: GLYCERIN; CARBOMER HOMOPOLYMER, UNSPECIFIED TYPE; WATER; TROLAMINE

Dr. Jbourne Daily Aegis Hand Clean Gel(Ethanol)30 ml POUCH X 10 :59545-0365